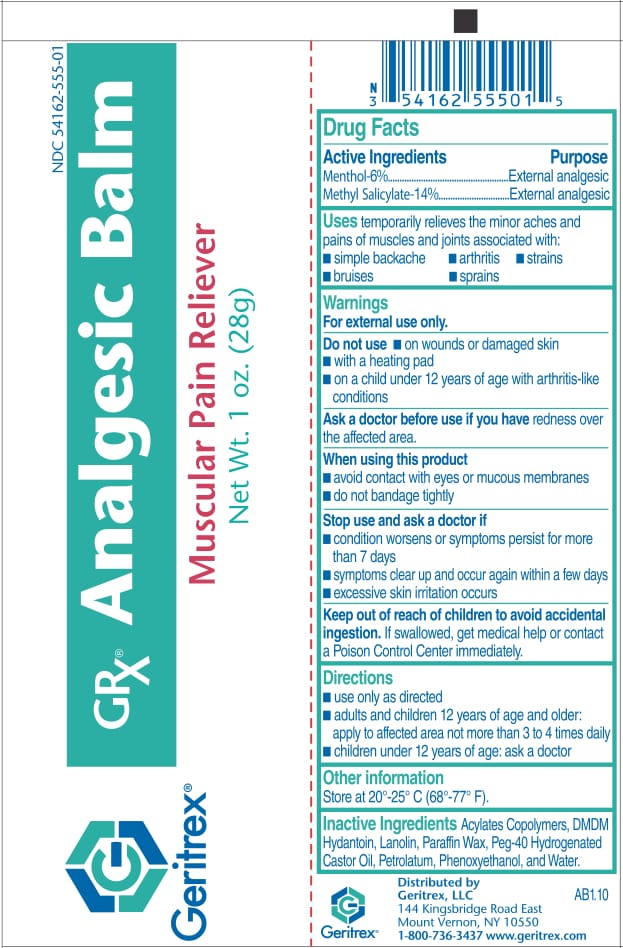 DRUG LABEL: Analgesic Balm
NDC: 54162-555 | Form: OINTMENT
Manufacturer: Geritrex LLC
Category: otc | Type: HUMAN OTC DRUG LABEL
Date: 20170919

ACTIVE INGREDIENTS: MENTHOL 1.74 g/29 g; METHYL SALICYLATE 4.06 g/29 g
INACTIVE INGREDIENTS: DMDM HYDANTOIN; WATER; LANOLIN; PARAFFIN; POLYOXYL 40 HYDROGENATED CASTOR OIL; PETROLATUM; PHENOXYETHANOL; CARBOMER COPOLYMER TYPE A

Analgesic Balm

Drug Facts

Menthol-6%, Methyl Salicylate-14%
Purpose: External analgesic

Uses

For the temporary relief of
minor aches and pain of muscles
and joints.

Directions

Adults and children
2 years of age and older: Apply
generously to affected area not
more than 3 to 4 times daily.
Children under 2 years of age:
Consult a doctor.

DOSAGE AND ADMINISTRATION

Apply generously to affected area not
more than 3 to 4 times daily.
Children under 2 years of age:
Consult a doctor.

WARNINGS

Avoid contact with eyes or
mucous membranes. Discontinue
use if excessive irritation of the
skin develops.
• Do not: bandage tightly; apply
to wounds, damaged skin, or
use with a heating pad.
• If condition worsens, or if
symptoms persist more than
7 days or clear-up and reoccur
again within a few days,
discontinue use of this product
and consult a doctor. If
swallowed, get medical help
or contact a Poison Control
Center immediately.

INACTIVE INGREDIENT

Acylates Copolymer, DMDM Hydantoin,
Lanolin, Paraffin Wax,
Peg-40 Hydrogenated Castor Oil,
Petrolatum, Phenoxyethanol, Water.

STORAGE

At room temperature
20º-25º C (68º-77º F). Close cap
tightly after use.

OTC - KEEP OUT OF REACH OF CHILDREN

Children under 2 years of age:
Consult a doctor.